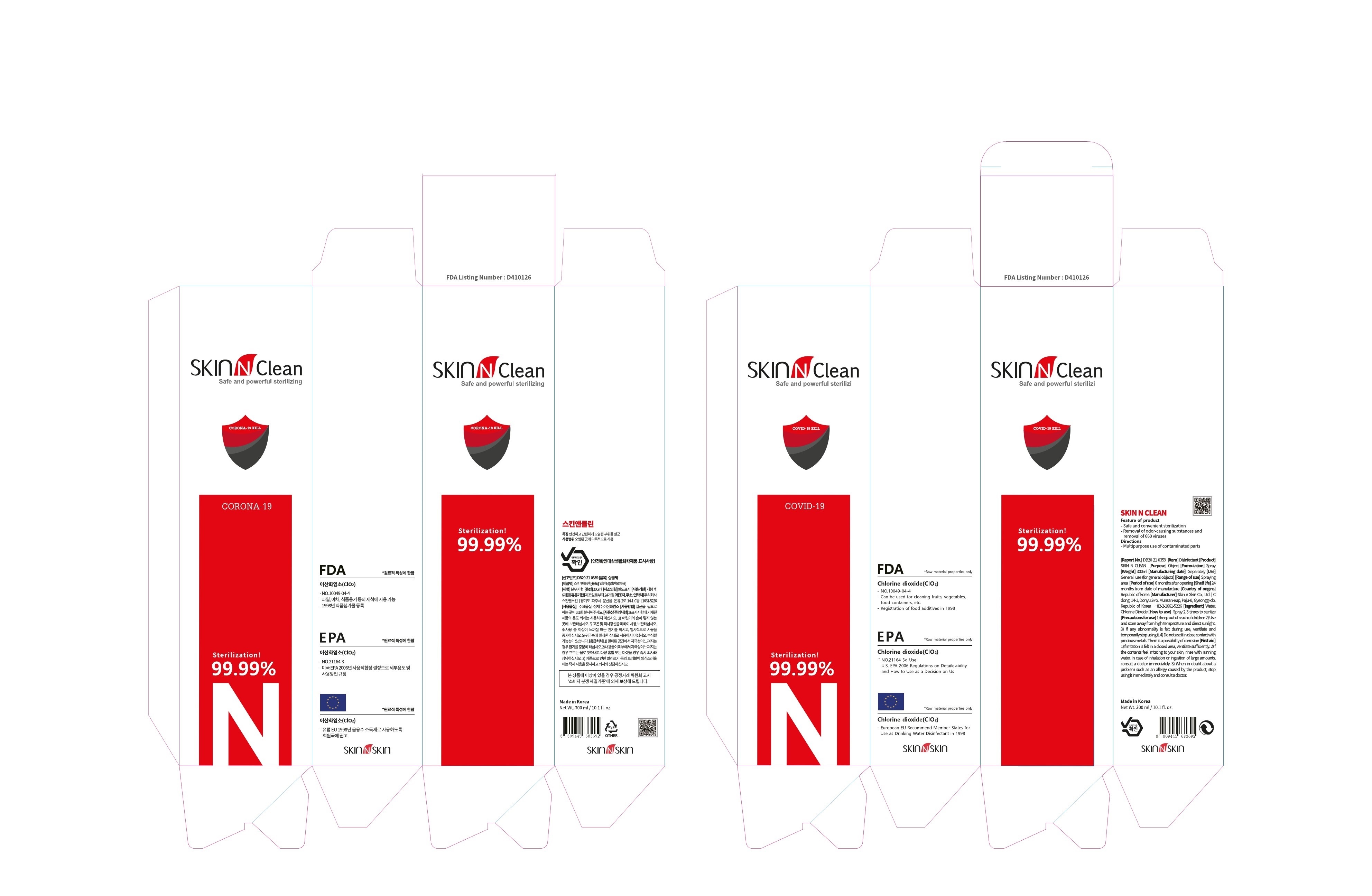 DRUG LABEL: SKIN N CLEAN
NDC: 74674-0007 | Form: LIQUID
Manufacturer: Skin n Skin Co., Ltd.
Category: otc | Type: HUMAN OTC DRUG LABEL
Date: 20201025

ACTIVE INGREDIENTS: CHLORINE DIOXIDE 0.01 g/100 mL
INACTIVE INGREDIENTS: WATER

Skin n Skin Co., Ltd. - Protect By Hand Sanitizer Water (Ethanol)

ACTIVE INGREDIENT

chlorine dioxide

INACTIVE INGREDIENT

water

PURPOSE

antiseptic

keep out of reach of the children

INDICATIONS AND USAGE

spray where needed

WARNINGS

For external use only. Flammable. Keep away from heat or flame.

Do not use

- in children less than 2 months of age
- on open skin wounds

When using this product keep out of eyes, ears, and mouth. In case of contact with eyes, rinse thoroughly with water.

Stop use and ask a doctor if irritation or rash occurs. These may be signs of a serious condition.

Keep out of reach of children. If swallowed, get medical help or contact a Poison Control Center right away.

DOSAGE AND ADMINISTRATION

for external use only